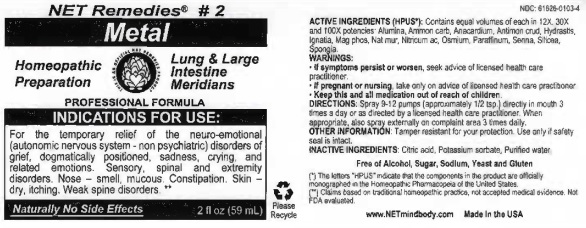 DRUG LABEL: Metal
NDC: 61626-0103 | Form: LIQUID
Manufacturer: NET Remedies
Category: homeopathic | Type: HUMAN OTC DRUG LABEL
Date: 20210119

ACTIVE INGREDIENTS: ALUMINUM OXIDE 12 [hp_X]/59 mL; AMMONIUM CARBONATE 12 [hp_X]/59 mL; ANACARDIUM OCCIDENTALE FRUIT 12 [hp_X]/59 mL; ANTIMONY TRISULFIDE 12 [hp_X]/59 mL; GOLDENSEAL 12 [hp_X]/59 mL; STRYCHNOS IGNATII SEED 12 [hp_X]/59 mL; MAGNESIUM PHOSPHATE, DIBASIC 12 [hp_X]/59 mL; SODIUM CHLORIDE 12 [hp_X]/59 mL; NITRIC ACID 12 [hp_X]/59 mL; OSMIUM 12 [hp_X]/59 mL; PARAFFIN 12 [hp_X]/59 mL; SENNA LEAF 12 [hp_X]/59 mL; SILICON DIOXIDE 12 [hp_X]/59 mL; SPONGIA OFFICINALIS SKELETON, ROASTED 12 [hp_X]/59 mL
INACTIVE INGREDIENTS: CITRIC ACID MONOHYDRATE; POTASSIUM SORBATE; WATER

Metal

ACTIVE INGREDIENT

ACTIVE INGREDIENTS (HPUS*): Contains equal volumes of each in 12X, 30X, and 100X potencies: Aluminia, Ammon carb, Anacardium, Antimon crud, Hydrastis, Ignatia, Mag phos, Nat mur, Nitricum ac, Osmium, Paraffinum, Senna, Silicea, Spongia.

(*) The letters "HPUS" indicate that the components in the product are officially monographed in the Homeopathic Pharmacopeia of the United States.

(**) Claims based on traditional homeopathic practice, not accepted medical evidence. Not FDA evaluated.

INDICATIONS FOR USE:

For the temporary relief of the neuro-emotional (autonomic nervous system - non psychiatric) disorders of grief, dogmatically positioned, sadness, crying, and related emotions. Sensory, spinal and extremity disorders. Nose - smell, mucous. Constipation. Skin - dry, itching. Weak spine disorders.**

WARNINGS:

• If symptoms oersist or worsen, seek advice of licensed health care practicioner.

• If pregnant or nursing, take only on advice of licensede health care practicioner.

• Keep this and all medication out of reach of children.

KEEP OUT OF REACH OF CHILDREN

• Keep this and all medication out of reach of children.

DOSAGE AND ADMINISTRATION

DIRECTIONS: Spray 9-12 pumps (approximately 1/2 tsp.) directly in mouth 3 times a day or as directed by licensed health care practicioner. When approprate, also spray externally on complaint area 3 times daily.

OTHER INFORMATION: Tamper resistant for your protection. Use only if safety seal is intact.

INACTIVE INGREDIENTS: Citrid acid, Potassium sorbate, Purified Water.

Free of Alcohol, Sugar, Sodium, Yeast and Gluten.

QUESTIONS

www.NETmindbody.com

Made in the USA

PACKAGE LABEL

NET Remedies #2

Metal

Homeopathic Preparation

Lung & Large Intestine Meridans

PROFESSIONAL FORMULA

Naturally No Side Effects

PURPOSE

For the temporary relief of the neuro-emotional (autonomic nervous system - non psychiatric) disorders of grief, dogmatically positioned, sadness, crying, and related emotions. Sensory, spinal and extremity disorders. Nose - smell, mucous. Constipation. Skin - dry, itching. Weak spine disorders.**